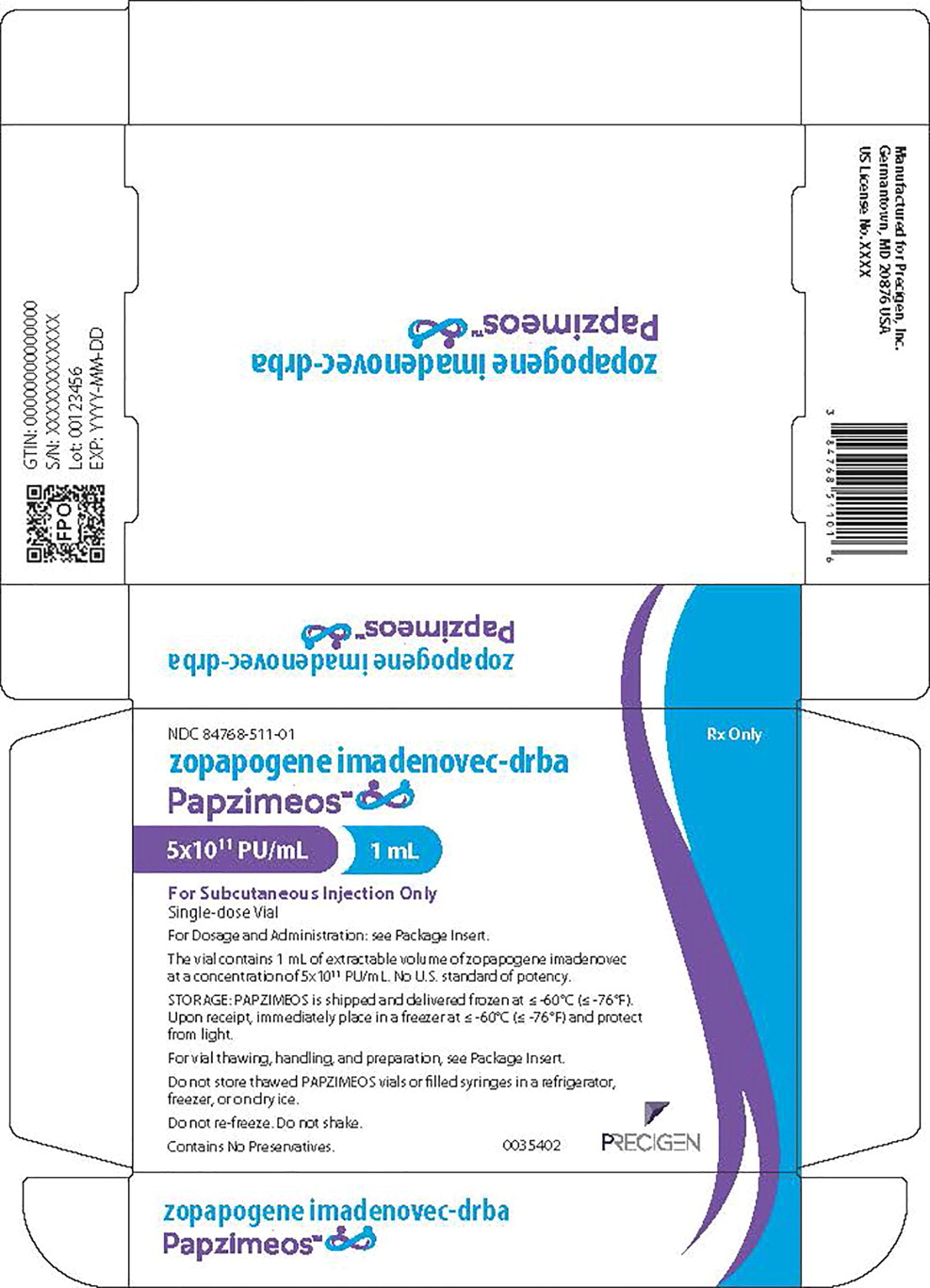 DRUG LABEL: PAPZIMEOS
NDC: 84768-511 | Form: INJECTION, SUSPENSION
Manufacturer: Precigen, Inc.
Category: prescription | Type: HUMAN PRESCRIPTION DRUG LABEL
Date: 20250812

ACTIVE INGREDIENTS: ZOPAPOGENE IMADENOVEC 500000000000 {VP}/1 mL
INACTIVE INGREDIENTS: tromethamine; sodium chloride; magnesium chloride; polysorbate 80; trehalose dihydrate

HIGHLIGHTS OF PRESCRIBING INFORMATION

These highlights do not include all the information needed to use PAPZIMEOS™ safely and effectively. See full prescribing information for PAPZIMEOS.
PAPZIMEOS (zopapogene imadenovec-drba) suspension for subcutaneous injection
Initial U.S. Approval: 2025

1 INDICATIONS AND USAGE

PAPZIMEOS™ is a non-replicating adenoviral vector-based immunotherapy indicated for the treatment of adults with recurrent respiratory papillomatosis. (1)

2 DOSAGE AND ADMINISTRATION

PAPZIMEOS is for subcutaneous injection only. (2.1)

The recommended dose of PAPZIMEOS is 5×10^11 particle units (PU) per injection administered by subcutaneous injection four (4) times over a 12-week interval. (2.1)

Prior to the initial administration of PAPZIMEOS, perform a surgical debulking of visible papilloma to establish minimal residual disease. To maintain minimal residual disease during treatment with PAPZIMEOS, remove visible papilloma, if present, prior to the third and fourth administration of PAPZIMEOS. (2.1)

3 DOSAGE FORMS AND STRENGTHS

PAPZIMEOS is supplied in a single-dose vial that contains 5×10^11 PU in an extractable volume of 1 mL of suspension. (3)

4 CONTRAINDICATIONS

None. (4)

5 WARNINGS AND PRECAUTIONS

- Injection-site reactions: Injection-site reactions, have been observed. Monitor patients for local site reactions for at least 30 minutes after the initial treatment. (5.1)
- Thrombotic events: Thrombotic events may occur following administration of adenoviral vector-based therapies. Monitor patients for signs and symptoms of thrombotic events and treat events according to clinical practice. (5.2)

6 ADVERSE REACTIONS

The most common adverse reactions (incidence ≥5%) were injection site reactions, fatigue, chills, pyrexia, myalgia, nausea, headache, tachycardia, diarrhea, vomiting, and hyperhidrosis. (6.1)

To report SUSPECTED ADVERSE REACTIONS, contact Precigen Inc. at 855-743-6777 and medinfo@precigen.com or FDA at 1-800-FDA-1088 or www.fda.gov/medwatch.

FULL PRESCRIBING INFORMATION

1 INDICATIONS AND USAGE

PAPZIMEOS is indicated for the treatment of adults with recurrent respiratory papillomatosis.

2 DOSAGE AND ADMINISTRATION

2.1 Recommended Dosage

PAPZIMEOS is for subcutaneous injection only.

The recommended dosage of PAPZIMEOS is 5×10^11 particle units (PU) per injection administered as subcutaneous injection four times over a 12-week interval. The recommended dosing schedule for PAPZIMEOS is shown in Table 1.

Table 1: Recommended Treatment Schedule for PAPZIMEOS
Administration | Administration Interval
Initial | --
Second | 2 weeks after initial administration^1
Third | 6 weeks after initial administration
Fourth | 12 weeks after initial administration
^1The second administration should occur no less than 11 days after the initial administration.

Prior to the initial administration of PAPZIMEOS, perform a surgical debulking of visible papilloma to establish minimal residual disease. To maintain minimal residual disease during treatment with PAPZIMEOS, remove visible papilloma, if present, prior to the third and fourth administration of PAPZIMEOS.

2.2 Preparation and Handling

PAPZIMEOS is a non-replicating adenoviral vector-based immunotherapy. Follow universal biosafety precautions for handling.

PAPZIMEOS is provided as a single-dose vial of sterile frozen suspension.

PAPZIMEOS MUST BE RAPIDLY thawed before use and prepared for immediate administration.

Once thawed, DO NOT place the PAPZIMEOS vial in a refrigerator, freezer, or on dry ice. Protect PAPZIMEOS from light. DO NOT shake the vial.

Recommended Supplies and Materials

1. Freezer for storage of PAPZIMEOS at temperature ≤ -60°C [≤ -76°F]
2. Water bath or dry bead bath set to 37°C [98.6°F]
3. 3 mL sterile syringe
4. Sterile needle (18G to 22G without a filter) to withdraw PAPZIMEOS from the vial
5. Sterile needle for subcutaneous injection (23G to 25G needle, 1/2 - 5/8 inch long)
6. 70% isopropyl alcohol pads

Receipt of PAPZIMEOS

PAPZIMEOS is provided as a sterile, frozen suspension that has been aseptically filled into single-dose vials fitted with a rubber stopper and aluminum flip-cap seal. Each vial is sealed inside a pouch, which is placed in the carton along with a Package Insert. The PAPZIMEOS carton is shipped frozen at ≤ -60°C [≤ -76°F] in an insulated shipping box containing dry ice. On receipt, the PAPZIMEOS carton must be stored in a freezer at ≤ -60°C [≤ -76°F].

Preparation of PAPZIMEOS for Injection

1. Remove the carton of PAPZIMEOS from the freezer when ready for administration.
2. Take the vial out of the pouch and immediately thaw in a 37°C [98.6°F] water bath or dry bead bath with the vial in an upright position until there are no visible ice crystals in the vial. Exposure of the thawed vial to the 37°C [98.6°F] water bath or dry bead bath should be less than or equal to 5 minutes.
3. Immediately after thawing, wipe the vial with 70% isopropyl alcohol. Flip off the cap and wipe the rubber stopper top.
4. Swirl gently and visually inspect the vial of PAPZIMEOS. PAPZIMEOS should appear as a slightly opalescent to opalescent, colorless liquid, and free of visible particulates. DO NOT use if particulates or discoloration are visible in the suspension.
5. Aseptically withdraw 1 mL of PAPZIMEOS from the thawed vial using a 3 mL syringe with an 18G to 22G needle. DO NOT use a filter needle.
6. Replace the 18G to 22G needle with a subcutaneous injection needle (23G to 25G).
7. Dispose of the used needle and empty vial in a biohazard container.

DO NOT hold PAPZIMEOS at room temperature for more than 60 minutes after thawing.

DO NOT store thawed PAPZIMEOS vials or filled syringes in a refrigerator, freezer, or on dry ice.

Treat any PAPZIMEOS spills with a virucidal agent (such as sodium hypochlorite with 0.5% active chlorine or 6% hydrogen peroxide) for 15 minutes. Dispose of any unused product or waste materials as per facility biohazard waste disposal procedure.

2.3 Administration

Administer PAPZIMEOS via subcutaneous injection with the following procedures:

1. Select the lateral regions of the upper arm and thigh for injection. Avoid areas of edema, potential infection, wounds, scars, or the site of a recent subcutaneous injection.
2. Clean the injection site thoroughly with an alcohol swab and allow at least 30 seconds to dry.
3. Inject PAPZIMEOS by inserting the needle at an angle to ensure delivery in the subcutaneous space.
4. Clean the area with an alcohol swab again, DO NOT massage the site of injection.
5. Place potentially contaminated materials from the injection site, including dressings, that may have the patient's bodily fluids/waste, in a sealable bag and dispose into regular trash. These precautions should be followed for 1-2 weeks after injection. Practice proper hand hygiene, such as hand washing, when coming into direct contact with patient body waste.
6. Avoid direct contact with the injection site (e.g., touching or scratching) and dressings for approximately 24 hours following treatment.

3 DOSAGE FORMS AND STRENGTHS

PAPZIMEOS is supplied as a slightly opalescent to opalescent, colorless suspension for subcutaneous injection with a concentration of 5×10^11 PU/mL. Each single-dose vial delivers a minimum extractable volume of 1 mL [see How Supplied/Storage and Handling (16)].

4 CONTRAINDICATIONS

None.

5 WARNINGS AND PRECAUTIONS

5.1 Injection-Site Reactions

Injection-site reactions have occurred with PAPZIMEOS injection. Monitor patients for local site reactions for at least 30 minutes after the initial treatment and manage accordingly.

5.2 Thrombotic Events

Thrombotic events may occur following administration of adenoviral vector-based therapies including PAPZIMEOS due to the potential to induce prothrombotic antibody development. Monitor patients for signs and symptoms of thrombotic events and treat events according to clinical practice.

6 ADVERSE REACTIONS

6.1 Clinical Trials Experience

Because clinical trials are conducted under widely varying conditions, adverse reaction rates observed in the clinical trials of a drug cannot be directly compared to rates in the clinical trials of another drug and may not reflect the rates observed in practice.

The safety data described in this section reflects exposure to PAPZIMEOS in one clinical study (Study PRGN-2012-201). A total of 38 adults with recurrent respiratory papillomatosis received a PAPZIMEOS dose of either 1×10^11 PU (n=3), or 5×10^11 PU (n=35) per injection on Days 1, 15, 43, and 85 [see Clinical Studies (14)]. The most common adverse reactions (incidence ≥5%) are summarized in Table 2.

Table 2: Adverse Reactions occurring in ≥5% of Patients in Study PRGN-2012-201 (N=38)
Preferred Term | Grade 1-2* n (%)
Injection site reaction | 37 (97)
Fatigue | 28 (74)
Chills | 25 (66)
Pyrexia | 24 (63)
Myalgia | 11 (29)
Nausea | 10 (26)
Headache | 4 (11)
Tachycardia | 3 (8)
Diarrhea | 2 (5)
Vomiting | 2 (5)
Hyperhidrosis | 2 (5)
*Graded per NCI CTCAE v5.0. There were no Grade >2 adverse reactions.

Other clinically significant adverse reactions occurring in <5% of patients included vision blurred (3%), injection site bruising (3%), dizziness (3%), dyspnea (3%), and pruritus (3%).

8 USE IN SPECIFIC POPULATIONS

8.1 Pregnancy

Risk Summary

There are no available data with PAPZIMEOS in pregnant women. Animal reproductive and developmental toxicity studies have not been conducted with PAPZIMEOS. In the PRGN-2012-201 study, one patient reported pregnancy at 6 months following completion of treatment with PAPZIMEOS. The patient delivered at 40 weeks without any reported birth complications or neonatal concerns.

In the U.S. general population, the estimated background risk of major birth defects and miscarriage in clinically recognized pregnancies is 2 to 4% and 15 to 20%, respectively.

8.2 Lactation

Risk Summary

There is no information available on the presence of PAPZIMEOS in human milk, the effects on the breastfed infant, or the effects on milk production. The developmental and health benefits of breastfeeding should be considered along with the mother's clinical need for PAPZIMEOS and any potential adverse effects on the breastfed child from PAPZIMEOS or from the underlying maternal condition.

8.4 Pediatric Use

The safety and effectiveness of PAPZIMEOS have not been established in pediatric patients.

8.5 Geriatric Use

There were 9 patients (24%) 65 years of age and older and 1 patient (3%) 75 years of age and older in Study PRGN-2012-201. Clinical studies of PAPZIMEOS did not include sufficient numbers of patients 65 years of age and older to determine whether they respond differently from younger patients.

11 DESCRIPTION

PAPZIMEOS (zopapogene imadenovec-drba) is a non-replicating adenoviral vector-based immunotherapy designed to express a fusion antigen comprising selected regions of human papillomavirus (HPV) types 6 and 11 proteins.

PAPZIMEOS has a concentration of 5×10^11 PU/mL. Each single-dose vial contains a minimum extractable volume of 1 mL and the following excipients: Tris base (10 mM), sodium chloride (75 mM), magnesium chloride hexahydrate (1 mM), polysorbate 80 (0.019 mM), and trehalose dihydrate (146 mM).

PAPZIMEOS is a sterile, slightly opalescent to opalescent colorless suspension.

The product contains no preservatives.

12 CLINICAL PHARMACOLOGY

12.1 Mechanism of Action

PAPZIMEOS is a non-replicating adenoviral vector-based immunotherapy designed to express a fusion antigen of selected regions of human papillomavirus (HPV) proteins expressed in HPV 6- and HPV 11-infected cells. PAPZIMEOS is designed to generate an immune response directed against HPV 6 and HPV 11 proteins in patients with recurrent respiratory papillomatosis.

12.2 Pharmacodynamics

The pharmacodynamic effect of PAPZIMEOS was evaluated in Study PRGN-2012-201 [see Clinical Studies (14)]. In 28 patients evaluated at completion of treatment, the induction of HPV 6- and HPV 11-specific T cell responses in RRP patients, was higher in RRP patients demonstrating a clinical response to treatment, i.e. reduction in or elimination of the requirement for surgical debulking during the 12 months following completion of treatment, with mean fold-change from baseline of 164.9 versus 5.1 (p<0.018). This difference persisted at 12 weeks post-treatment, with mean fold-change of 61.5 in responders versus 11.5 in non-responders.

12.3 Pharmacokinetics

No biodistribution and vector shedding studies have been conducted with PAPZIMEOS.

13 NONCLINICAL TOXICOLOGY

13.1 Carcinogenesis, Mutagenesis, Impairment of Fertility

No animal studies have been performed to evaluate the effects of PAPZIMEOS on carcinogenesis, mutagenesis, or impairment of fertility.

14 CLINICAL STUDIES

The efficacy of PAPZIMEOS was evaluated in an open-label, single-arm study in adults with recurrent respiratory papillomatosis (PRGN-2012-201; NCT04724980). The study enrolled adults who had histological and clinically diagnosed recurrent respiratory papillomatosis and had 3 or more debulking procedures to remove laryngotracheal papillomas in the 12 months prior to treatment with PAPZIMEOS.

A total of 38 patients received subcutaneous injections of PAPZIMEOS on days 1, 15, 43, and 85. Prior to initiation of treatment with PAPZIMEOS (Day 1), patients underwent a standard-of-care surgical debulking procedure to remove laryngotracheal papillomas. Physicians also had the option to remove any visible papillomas during the treatment interval. Of the 38 patients, 3 patients were treated with PAPZIMEOS at a dose of 1×10^11 particle units (PU) per injection. Thirty-five patients were treated at a dose of 5×10^11 PU per injection and were included in the efficacy evaluation.

The demographic characteristics of the population were as follows: the median age was 50 years (range 20 to 88 years), 15 patients (39%) were female, 33 patients (87%) were White, 1 patient (3%) was Asian, 1 patient (3%) was African American, 1 patient (3%) was of “other” race, 2 patients (5%) were of unknown race, and 32 patients (84%) were non-Hispanic or Latino. The mean (SD) BMI was 28 (6) kg/m^2. The median number of baseline surgical procedures performed in the 12 months prior to treatment was 4 (range 3 to 10). This included the protocol mandated debulking surgery on Day 1 to establish minimal residual disease.

The primary efficacy endpoint was the percentage of patients with a complete response to PAPZIMEOS treatment, defined as no requirement for surgical intervention in the 12 months after treatment.

At a dose of 5×10^11 PU per injection, 18 out of 35 patients achieved a complete response at 12 months resulting in a complete response rate of 51% [95% confidence interval (CI) 34 to 69%]. Of the 18 patients with a complete response in the ongoing study, 15 demonstrated continued complete response at 24 months yielding a complete response rate of 43% (95% CI 26 to 61%) at 2 years for the 35 patients in the efficacy population.

At a dose of 1×10^11 PU per injection, no patient (0 out of 3) achieved a complete response.

16 HOW SUPPLIED/STORAGE AND HANDLING

16.1 How Supplied

Each carton of PAPZIMEOS (NDC 84768-511-01) contains one single-dose vial (NDC 84768-511-99) of PAPZIMEOS sterile frozen suspension.

PAPZIMEOS is supplied in a single-dose vial made from cyclic olefin polymer (COP) with a rubber stopper and aluminum flip-cap seal. Each vial is sealed inside a pouch (NDC 84768-511-00). The pouch is placed in the container along with a Package Insert. Each vial is formulated to contain an extractable dose of 5×10^11 PU in a 1 mL suspension.

16.2 Storage and Handling

PAPZIMEOS is shipped and stored frozen at ≤ -60°C [≤ -76°F] and should be stored in an appropriate freezer at ≤ -60°C [≤ -76°F] until ready to thaw and administer.

DO NOT place the vial in a refrigerator, freezer, or on dry ice at any time once removed from the pouch. Protect the vials from light. DO NOT shake the vial.

PAPZIMEOS should not be held at room temperature for more than 60 minutes after thawing.

PAPZIMEOS is a non-replicating adenoviral vector-based immunotherapy. Follow universal biohazard precautions for handling [see Dosage and Administration (2.2)(2.3)] and for the disposal of all vials and syringes.

17 PATIENT COUNSELING INFORMATION

Discuss following with the patients.

- Injection Site Reactions: Inform patients injection site reactions have occurred after PAPZIMEOS injection. Signs and Symptoms may include reactions such as redness, pain, swelling, itching, or warmth at the injection site. Advise patients to manage symptoms with cold compresses, over the counter pain relievers or antihistamines, if needed. Seek medical care if symptoms worsen or are accompanied by signs of a systemic allergic reaction (difficulty breathing, widespread rash, facial swelling) or infection [see Warnings and Precautions (5.1)].
- Thrombotic Events: Inform patients that thrombotic events may occur after PAPZIMEOS injection. Signs and Symptoms may include shortness of breath, chest pain, leg swelling, persistent abdominal pain, or neurological symptoms (including severe or persistent headaches or blurred vision). Monitor patients for signs and symptoms of thrombotic events and treat events according to clinical practice [see Warnings and Precautions (5.2)].

Manufactured by:

Precigen, Inc.

20358 Seneca Meadows Parkway

Germantown, MD 20876 USA

U.S. License No. 2364

Principal Display Panel – 1 mL Carton Label

NDC 84768-511-01

Rx Only

zopapogene imadenovec-drba

Papzimeos™

5x10^11 PU/mL 1 mL

For Subcutaneous Injection Only

Single-dose Vial

For Dosage and Administration: See Package Insert.

The vial contains 1 mL of extractable volume of zopapogene imadenovec
at a concentration of 5x10^11 PU/mL. No U.S. standard of potency.

STORAGE: PAPZIMEOS is shipped and delivered frozen at ≤-60°C (≤-76°F).
Upon receipt, immediately place in a freezer at ≤-60°C (≤-76°F) and protect
from light.

For vial thawing, handling, and preparation, see Package Insert.

Do not store thawed PAPZIMEOS vials or filled syringes in a refrigerator,
freezer, or on dry ice.

Do not re-freeze. Do not shake.

Contains No Preservatives.

0035402

PRECIGEN